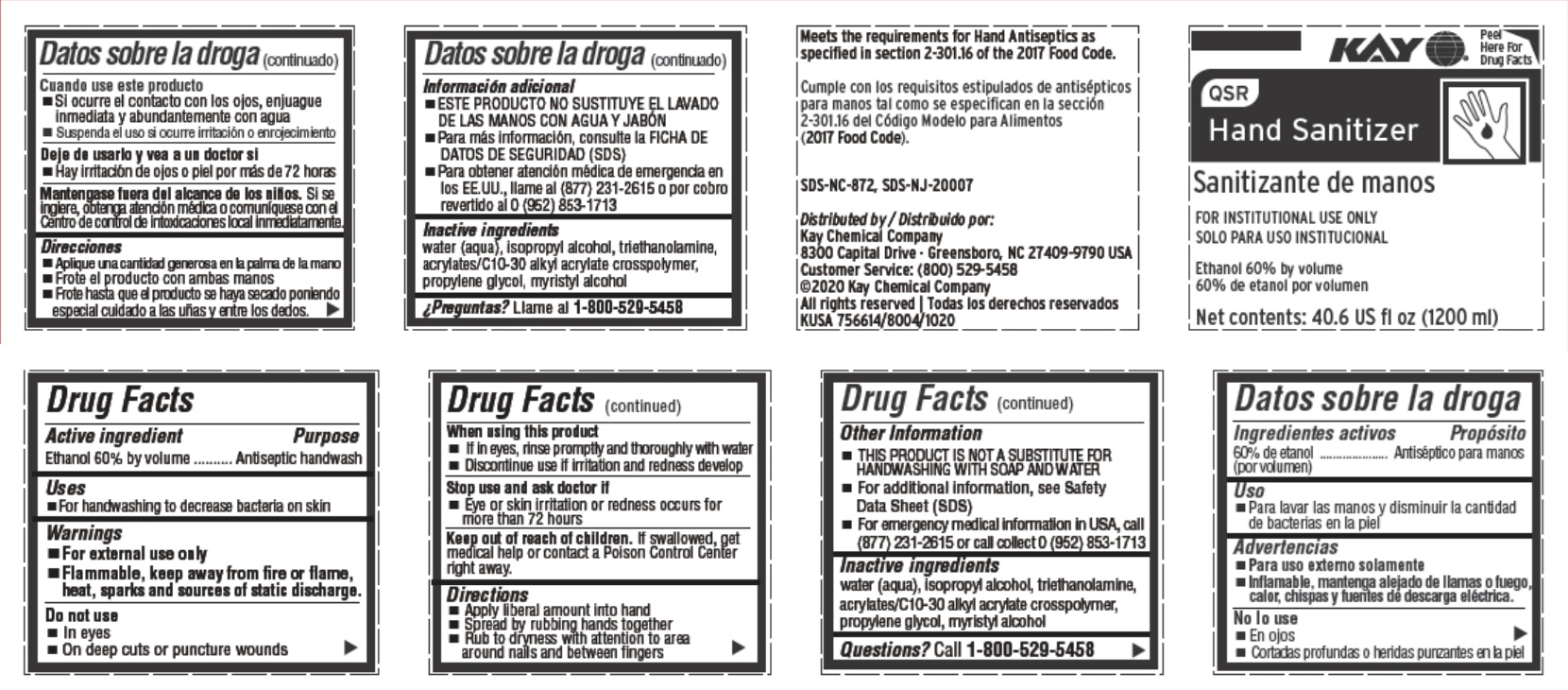 DRUG LABEL: QSR Hand Sanitizer
NDC: 47593-673 | Form: SOLUTION
Manufacturer: Ecolab Inc.
Category: otc | Type: HUMAN OTC DRUG LABEL
Date: 20251231

ACTIVE INGREDIENTS: ALCOHOL 60 mL/100 mL
INACTIVE INGREDIENTS: WATER; ISOPROPYL ALCOHOL; TROLAMINE; CARBOMER COPOLYMER TYPE B (ALLYL PENTAERYTHRITOL CROSSLINKED); PROPYLENE GLYCOL; MYRISTYL ALCOHOL

Drug Facts

Active ingredient

Ethanol 60% by volume

Purpose

Antiseptic handwash

Uses

- For handwashing to decrease bacteria on skin

Warnings

- For external use only.
- Flammable, keep away from fire or flame, heat, sparks and sources of static discharge.

Do not use

- In eyes
- on deep cuts or puncture wounds

When using this product

- If in eyes, rinse promptly and thoroughly with water
- Discontinue use if irritation and redness develop

Stop use and ask a doctor if

- Eye or skin irritation or redness occurs for more than 72 hours

Keep out of reach of children. If swallowed, get medical help or contact a Poison Control Center right away.

Directions

- Apply a liberal amount into hand
- Spread by rubbing hands together
- Rub to dryness with attention to area around nails and between fingers

Other information

- THIS PRODUCT IS NOT A SUBSTITUTE FOR HANDWASHING WITH SOAP AND WATER
- For additional information, see Safety Data Sheet (SDS)
- For emergency medical information in USA, call (877) 231-2615 or call collect 0 (952) 853-1713

Inactive ingredients

water (aqua), isopropyl alcohol, triethanolamine, acrylates/C10-30 alkyl acrylate crosspolymer, propylene glycol, myristyl alcohol

Questions? Call 1-800-529-5458

Principal display panel and representative label

KAY

QSR

Hand Sanitizer

FOR INSTITUTIONAL USE ONLY

Ethanol 60% by volume

Net contents: 40.6 US fl oz (1200 mL)

Meets the requirements for Hand Antiseptics as specified in section 2-301.16 of the 2017 Food Code.

(2017 Food Code).

SDS-NC-872, SDS-NJ-20007

Distributed by

Kay Chemical Company

8300 Capital Drive · Greensboro, NC 27409-9790 USA Customer Service: (800) 529-5458

©2020 Kay Chemical Company

All rights reserved | KUSA 756614/8004/1020